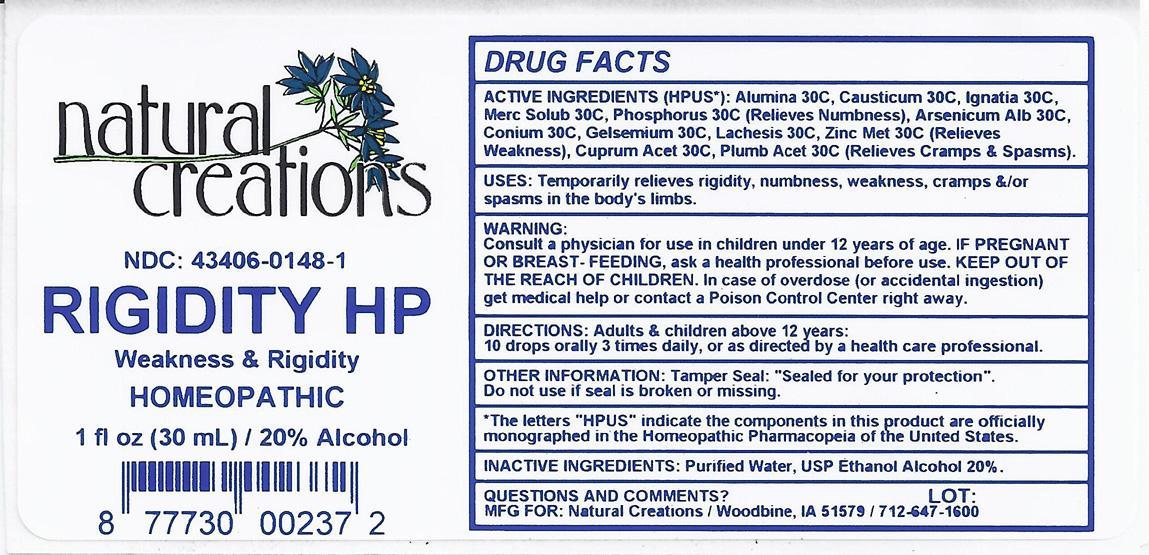 DRUG LABEL: RIGIDITY HP
NDC: 43406-0035 | Form: LIQUID
Manufacturer: Natural Creations, Inc.
Category: homeopathic | Type: HUMAN OTC DRUG LABEL
Date: 20121109

ACTIVE INGREDIENTS: ALUMINUM OXIDE 30 [hp_C]/1 mL; ARSENIC TRIOXIDE 30 [hp_C]/1 mL; CAUSTICUM 30 [hp_C]/1 mL; CONIUM MACULATUM FLOWERING TOP 30 [hp_C]/1 mL; CUPRIC ACETATE 30 [hp_C]/1 mL; GELSEMIUM SEMPERVIRENS ROOT 30 [hp_C]/1 mL; STRYCHNOS IGNATII SEED 30 [hp_C]/1 mL; LACHESIS MUTA VENOM 30 [hp_C]/1 mL; MERCURIUS SOLUBILIS 30 [hp_C]/1 mL; PHOSPHORUS 30 [hp_C]/1 mL; LEAD 30 [hp_C]/1 mL; ZINC 30 [hp_C]/1 mL
INACTIVE INGREDIENTS: WATER; ALCOHOL

RIGIDITY HP

ACTIVE INGREDIENT

ACTIVE INGREDIENTS (HPUS*): Alumina 30C, Arsenicum Album 30C, Causticum 30C, Conium Maculatum 30C, Cuprum Aceticum 30C, Gelsemium Sempervirens 30C, Ignatia Amara 30C, Lachesis Mutus 30C, Mercurius Solubilis 30C, Phosphorus 30C, Plumbum Aceticum 30C, Zincum Metallicum 30C

INDICATIONS AND USAGE

USES: Temporarily relieves rigidity, numbness, weakness, cramps &/or spasms in the body's limbs.

WARNING:

Consult a physician for use in children under 12 years of age. IF PREGNANT OR BREAST-FEEDING, ask a health care professional before use. KEEP OUT OF THE REACH OF CHILDREN. In case of overdose (or accidental ingestion) get medical help or contact a Poison Control Center right away.

DOSAGE AND ADMINISTRATION

DIRECTIONS: Adults and children above 12 years: 10 drops orally 3 times daily, or as directed by a health care professional.

OTHER INFORMATION: Tamper Seal: "Sealed for your protection."

Do not use if seal is broken or missing.

REFERENCES

*The letters "HPUS" indicate the components in the product are officially monographed in the Homeopathic Pharmacopeia of the United States.

INACTIVE INGREDIENTS: Purified Water, USP Ethanol Alcohol 20%

QUESTIONS AND COMMENTS?

MFG FOR: Natural Creations / Woodbine, IA / 51579 712.647.1600

LOT:

PURPOSE

USES: Temporarily relieves rigidity, numbness, weakness, cramps &/or spasms in the body's limbs.

KEEP OUT OF REACH OF CHILDREN

KEEP OUT OF THE REACH OF CHILDREN. In case of overdose (or accidental ingestion) get medical help or contact a Poison Control Center.

PACKAGE LABEL

NDC: 43406-0035-1

RIGIDITY HP

Weakness & Rigidity

HOMEOPATHIC

1 fl oz (30 mL) / 20% Alcohol

UPC: 877730002372